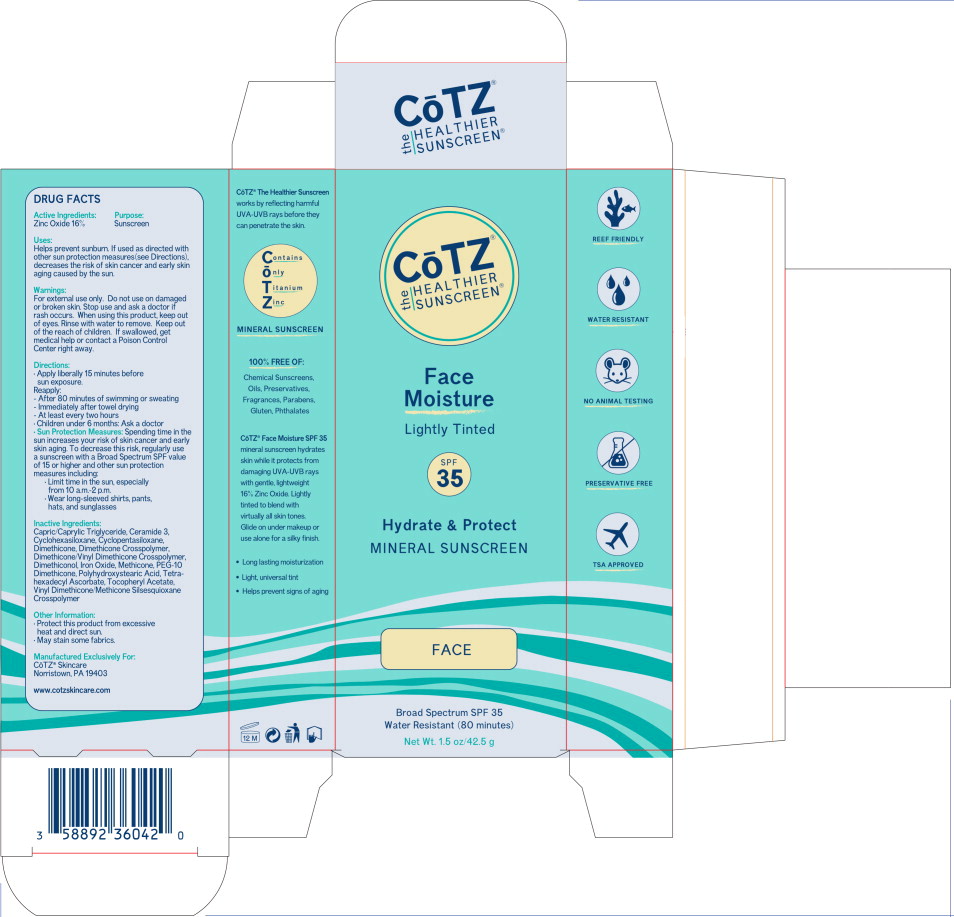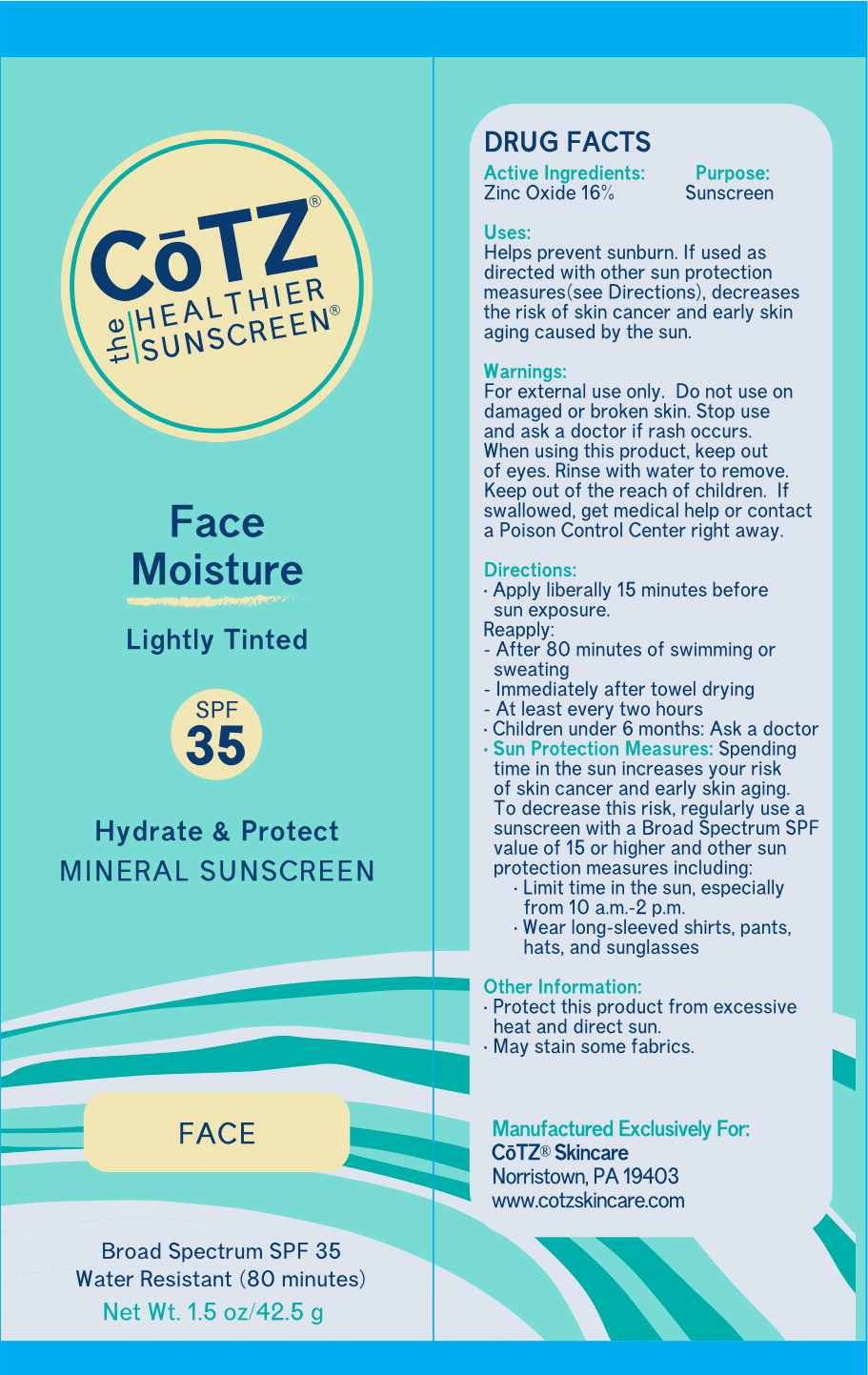 DRUG LABEL: CoTZ Face Moisture
NDC: 58892-360 | Form: CREAM
Manufacturer: Fallien Cosmeceuticals, LTD
Category: otc | Type: HUMAN OTC DRUG LABEL
Date: 20250109

ACTIVE INGREDIENTS: Zinc Oxide 160 mg/1 g
INACTIVE INGREDIENTS: MEDIUM-CHAIN TRIGLYCERIDES; CERAMIDE NP; Cyclomethicone 6; Cyclomethicone 5; Dimethicone 20; Dimethicone Crosspolymer (450000 MPA.S AT 12% in Cyclopentasiloxane); Dimethicone/Vinyl Dimethicone Crosspolymer (Soft Particle); Dimethiconol (2000 CST); Brown Iron Oxide; Hydrogen Dimethicone (20 CST); PEG-10 Dimethicone (600 CST); POLYHYDROXYSTEARIC ACID (2300 MW); VINYL DIMETHICONE/METHICONE SILSESQUIOXANE CROSSPOLYMER

Drug Facts

Active Ingredients:

Zinc Oxide 16%

Purpose:

Sunscreen

Uses:

Helps prevent sunburn. If used as directed with other sun protection measures (see Directions), decreases the risk of skin cancer and early skin aging caused by the sun.

Warnings:

KEEP OUT OF REACH OF CHILDREN

For external use only. Do not use on damaged or broken skin. Stop use and ask a doctor if rash occurs. When using this product, keep out of eyes. Rinse with water to remove. Keep out of the reach of children. If swallowed, get medical help or contact a Poison Control Center right away.

Directions:

- Apply liberally 15 minutes before sun exposure.
- Reapply:
  - After 80 minutes of swimming or sweating
  - Immediately after towel drying
  - At least every two hours
- Children under 6 months: Ask a doctor
- Sun Protection Measures: Spending time in the sun increases your risk of skin cancer and early skin aging. To decrease this risk, regularly use a sunscreen with a Broad Spectrum SPF value of 15 or higher and other sun protection measures including:
  - Limit time in the sun, especially from 10 a.m.-2 p.m.
  - Wear long-sleeved shirts, pants, hats, and sunglasses

Inactive Ingredients:

Capric/Caprylic Triglyceride, Ceramide 3, Cyclohexasiloxane, Cyclopentasiloxane, Dimethicone, Dimethicone Crosspolymer, Dimethicone/Vinyl Dimethicone Crosspolymer, Dimethiconol, Iron Oxide, Methicone, PEG-10 Dimethicone, Polyhydroxystearic Acid, Vinyl Dimethicone/Methicone Silsesquioxane Crosspolymer

Other Information:

- Protect this product from excessive heat and direct sun
- May stain some fabrics

Manufactured Exclusively For:
CoTZ® Skincare
Norristown, PA 19403

www.cotzskincare.com

Principal Display Panel – Carton Label

CoTZ®
the HEALTHIER SUNSCREEN®

Face
Moisture

Lightly Tinted

SPF
35

Hydrate & Protect
MINERAL SUNCREEN

FACE

Broad Spectrum SPF 35

Water Resistant (80 Minutes)

Net Wt. 1.5 oz/42.5 g

Principal Display Panel – Tube Label

CoTZ®
the HEALTHIER SUNSCREEN®

Face
Moisture

Lightly Tinted

SPF
35

Hydrate & Protect
MINERAL SUNCREEN

FACE

Broad Spectrum SPF 35

Water Resistant (80 Minutes)

Net Wt. 1.5 oz/42.5 g